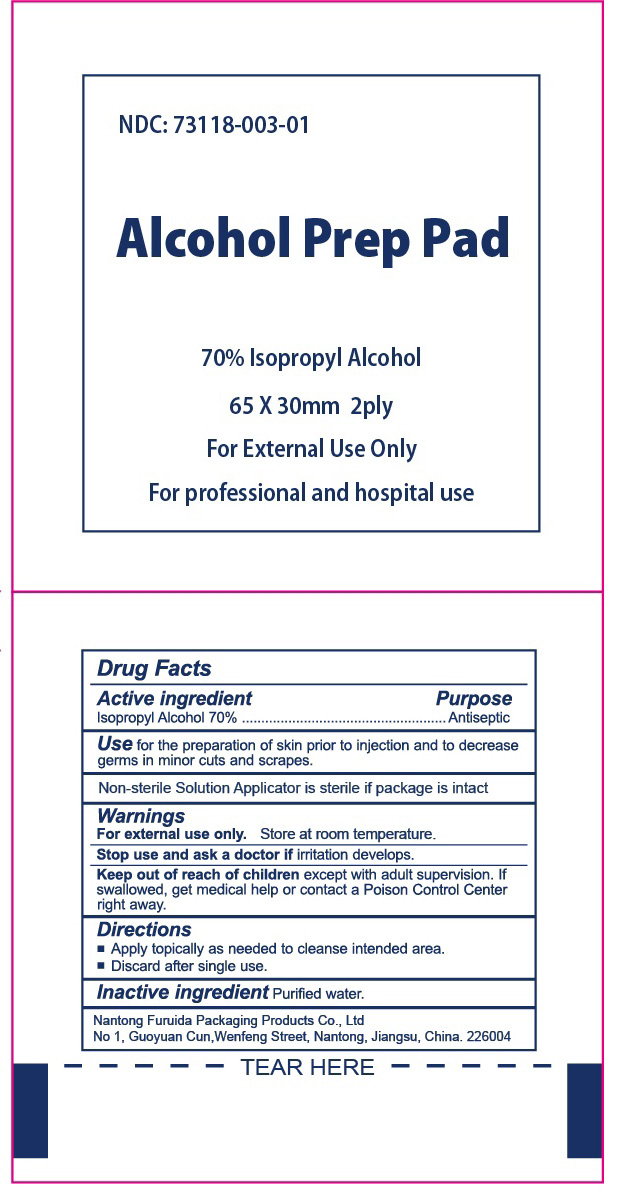 DRUG LABEL: Alcohol Prep Pad
NDC: 73118-003 | Form: SWAB
Manufacturer: Nantong Furuida Packaging Products Co., Ltd.
Category: otc | Type: HUMAN OTC DRUG LABEL
Date: 20210524

ACTIVE INGREDIENTS: ISOPROPYL ALCOHOL 0.7 mL/1 1
INACTIVE INGREDIENTS: WATER 0.3 mL/1 1

73118-003

Active Ingredient

Isopropyl Alcohol 70%

Purpose

Antiseptic

Use

For preparation of skin prior to injection prior to injection and to decrease germs in minor cuts and scrapes,

Warnning

For External use only.

Stop use and ask a doctor if irritation develops.

Keep out of reach of children except with adult supervision.

If swallowed,get medical help or contact a Poison Control Center right away.

Directions

Apply topically as needed to cleanse intended area.

Discard after single use.

Inactive Ingredients

Inactive Ingredients: Water